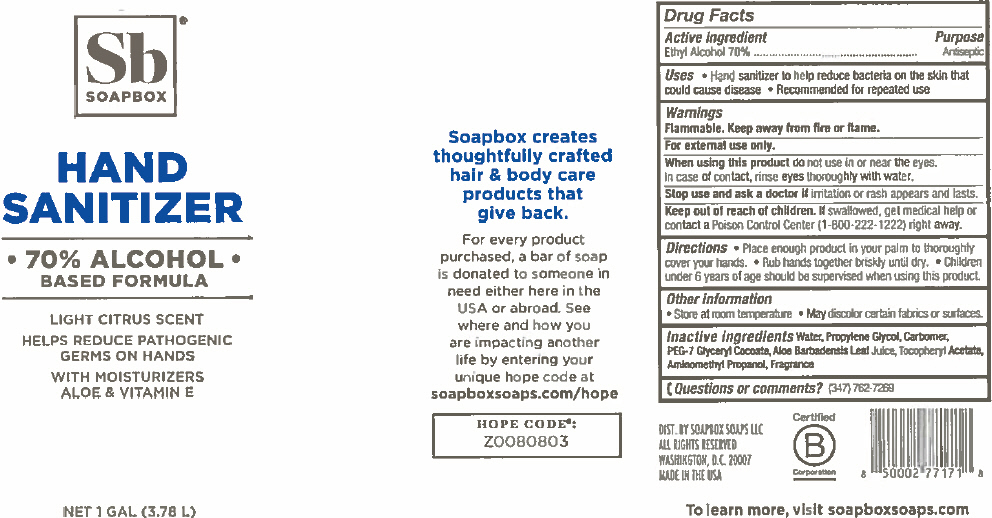 DRUG LABEL: Hand Sanitizer 
NDC: 75115-128 | Form: GEL
Manufacturer: Soapbox Soaps, LLC
Category: otc | Type: HUMAN OTC DRUG LABEL
Date: 20200731

ACTIVE INGREDIENTS: alcohol 70 mL/100 mL
INACTIVE INGREDIENTS: Propylene Glycol; water; CARBOMER HOMOPOLYMER TYPE C (ALLYL PENTAERYTHRITOL CROSSLINKED); PEG-7 Glyceryl Cocoate; .ALPHA.-TOCOPHEROL ACETATE; Aloe vera leaf; AminoMethylPropanol

Hand Sanitizer
70% Alcohol based formula

Drug Facts

Active Ingredient

Ethyl Alcohol 70%

Purpose

Antiseptic

Uses

- Hand sanitizer to help reduce bacteria on the skin that could cause disease
- recommended for repeated use

Warnings

Flammable. Keep away from fire or flame.

For external use only.

When using this product do not use in or near the eyes.

In case of contact, rinse eyes thoroughly with water.

Stop use and ask a doctor if irritation and rash appears and lasts.

Keep Out of reach of children. If swallowed get medical help or contact poison control center (1-800-222-1222) right away.

Directions

- Place enough product in your palm to thoroughly cover your hands.
- Rub hands together briskly until dry.
- Children under 6 years of age should be supervised when using this product.

Other Information

- store at room temperature
- may discolor certain fabrics or surfaces

Inactive Ingredients

Water, Propylene Glycol, Carbomer, PEG-7 Glyceryl Cocoate , Aloe Barbadensis Leaf Juice, Tocopheryl Acetate, Aminomethyl Propanol, Fragrance

Questions or Comments ?

1-347-762-7269

DIST. BY SOAPBOX SOAPS LLC
ALL RIGHTS RESERVED
WASHINGTON, D.C. 20007

PRINCIPAL DISPLAY PANEL - 3.78 L Bottle Label

SOAPBOX®

HAND
SANITIZER

• 70% ALCOHOL •
BASED FORMULA

LIGHT CITRUS SCENT

HELPS REDUCE PATHOGENIC
GERMS ON HANDS

WITH MOISTURIZERS
ALOE & VITAMIN E

NET 1 GAL (3.78 L)